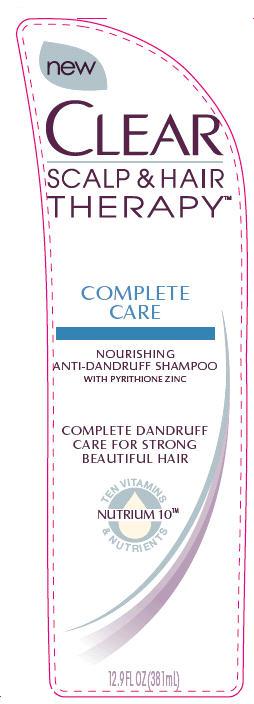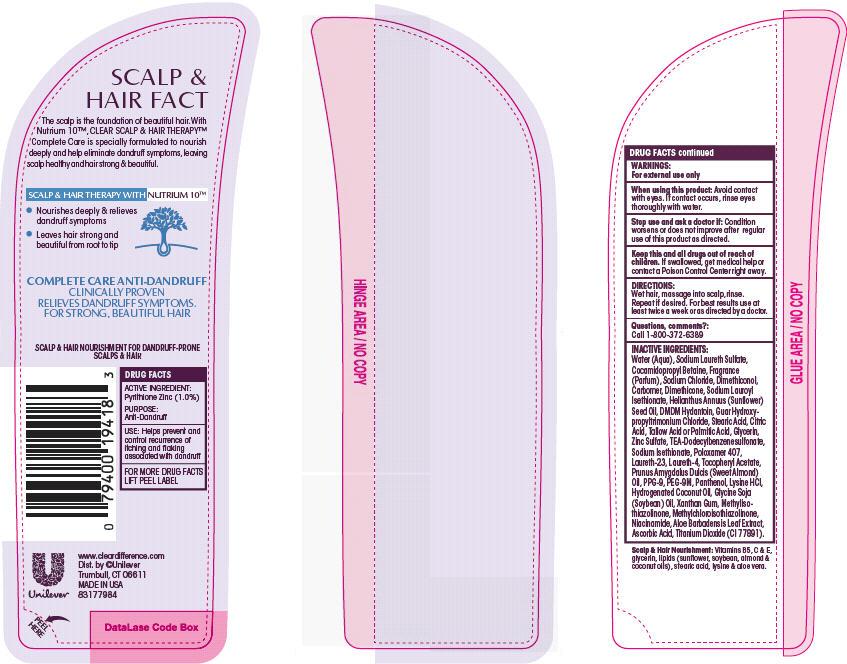 DRUG LABEL: Clear
NDC: 64942-1252 | Form: SHAMPOO
Manufacturer: Conopco Inc. d/b/a Unilever
Category: otc | Type: HUMAN OTC DRUG LABEL
Date: 20120503

ACTIVE INGREDIENTS: Pyrithione Zinc 1.0 mL/100 mL
INACTIVE INGREDIENTS: WATER; SODIUM LAURETH SULFATE; COCAMIDOPROPYL BETAINE; SODIUM CHLORIDE; TITANIUM DIOXIDE; SODIUM LAUROYL ISETHIONATE; DMDM HYDANTOIN; TEA-DODECYLBENZENESULFONATE; SUNFLOWER OIL; CITRIC ACID MONOHYDRATE; PPG-9; METHYLCHLOROISOTHIAZOLINONE; METHYLISOTHIAZOLINONE; NIACINAMIDE; GUAR HYDROXYPROPYLTRIMONIUM CHLORIDE (1.7 SUBSTITUENTS PER SACCHARIDE); STEARIC ACID; PALMITIC ACID; ZINC SULFATE; DIMETHICONOL (41 MPA.S); DIMETHICONE; SODIUM ISETHIONATE; POLOXAMER 407; LAURETH-23; LAURETH-4; .ALPHA.-TOCOPHEROL ACETATE, D-; ALMOND OIL; POLYETHYLENE GLYCOL 400000; PANTHENOL; LYSINE HYDROCHLORIDE; HYDROGENATED COCONUT OIL; SOYBEAN OIL; XANTHAN GUM; ALOE VERA LEAF; ASCORBIC ACID

Clear Complete Care Anti Dandruff Shampoo PDP and drug facts box

Active Ingredient

Pyrithione Zinc (1.0%)

Purpose
Antidandruff

INDICATIONS AND USAGE

Uses: helps prevent and control recurrence of itching and flaking associated with dandruff

Warnings
For external use only

When using this product: avoid contact with eyes. If contact occurs, rinse eyes thoroughly with water.

Stop use and ask a doctor if: Condition worsens or does not improve after regular use of this product as directed.

KEEP OUT OF REACH OF CHILDREN

Keep this and all drugs out of reach of children. If swallowed, get medical help or contact a Poison Control Center right away.

DOSAGE AND ADMINISTRATION

Directions: Wet hair, massage into scalp, rinse. Repeat if desired. For best results use at least twice a week or as directed by a doctor.

Inactive Ingredients
Water (Aqua)
Sodium Laureth Sulfate
Cocamidopropyl Betaine
Fragrance (Parfum)
Sodium Chloride
Dimethiconol
Carbomer
Dimethicone
Sodium Lauroyl Isethionate
Helianthus Annuus (Sunflower) Seed Oil
DMDM Hydantoin
Guar Hydroxypropyltrimonium Chloride
Stearic Acid
Citric Acid
Tallow Acid or Palmitic Acid
Zinc Sulfate
TEA-Dodecylbenzenesulfonate
Sodium Isethionate
Poloxamer 407
Laureth-23
Laureth-4
Tocopheryl Acetate
Prunus Amygdalus Dulcis (Sweet Almond) Oil
PPG-9
PEG-9M
Panthenol
Lysine HCl
Hydrogenated Coconut Oil
Glycine Soja (Soybean) Oil
Xanthan Gum
Methylisothiazolinone
Methylchloroisothiazolinone
Niacinamide
Aloe Barbadensis Leaf Extract
Ascorbic Acid
Titanium Dioxide (CI 77891)

Questions, comments?: 1-800-372-6389

PACKAGE LABEL

PDP front

PACKAGE LABEL

back